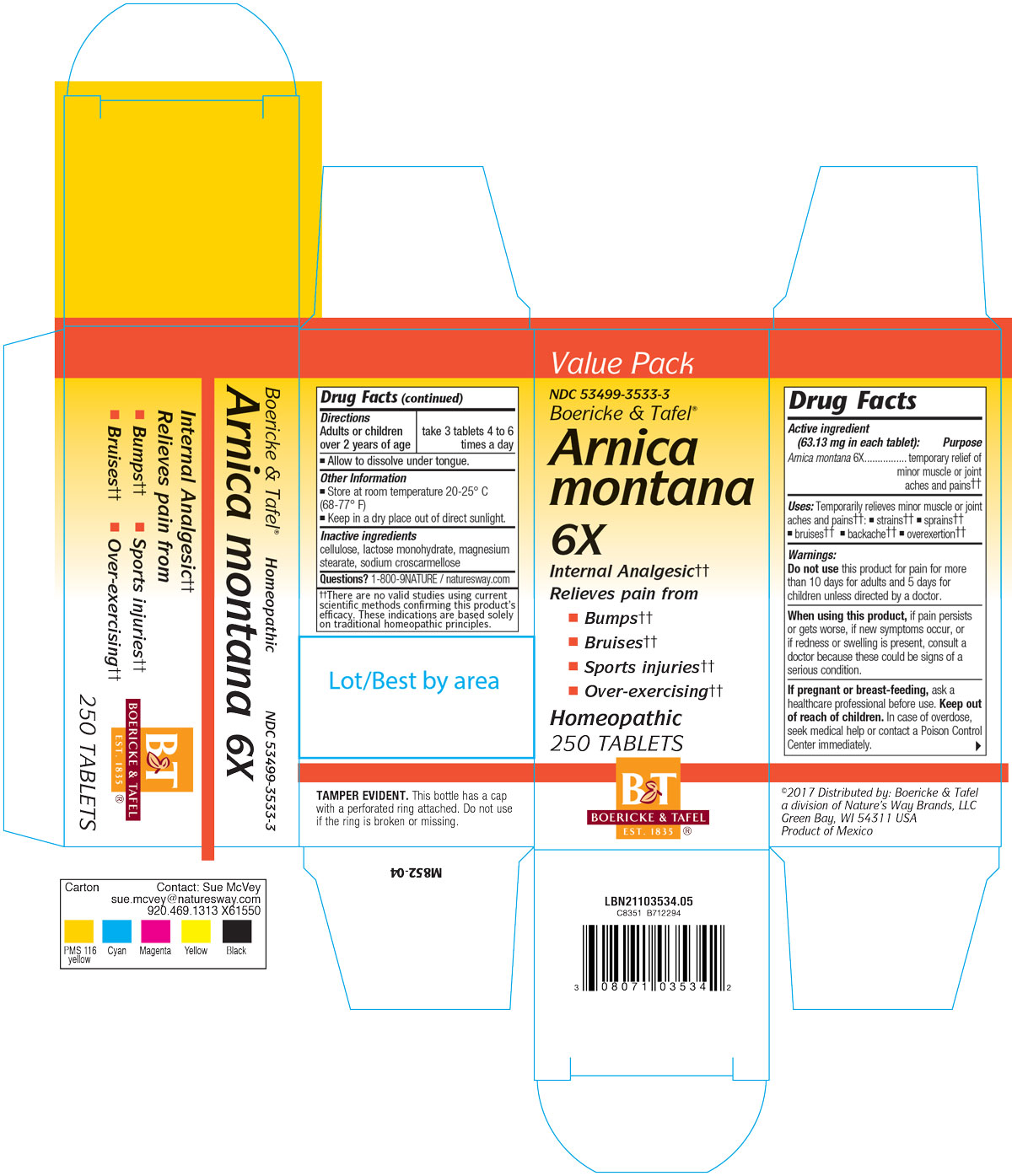 DRUG LABEL: Arnica Montana 6X
NDC: 68466-1043 | Form: TABLET
Manufacturer: Schwabe Mexico, S.A. de C.V.
Category: homeopathic | Type: HUMAN OTC DRUG LABEL
Date: 20201012

ACTIVE INGREDIENTS: ARNICA MONTANA 6 [hp_X]/1 1
INACTIVE INGREDIENTS: CELLULOSE, MICROCRYSTALLINE; LACTOSE MONOHYDRATE; MAGNESIUM STEARATE; CROSCARMELLOSE SODIUM

Arnica Montana 6X

Active Ingredient

Arnica montana 6X

Inactive Ingredients

CELLULOSE

LACTOSE MONOHYDRATE

MAGNESIUM STEARATE

SODIUM CROSCARMELLOSE

Dosage & Administration

Dosage:

Adults or children over 2 years: Take 3 tablets 4-6 times a day.

Allow to dissolve under tongue.

Indications

Temporarily relieves minor muscle or joint aches and pain; strains, sprains, bruises, backache or overexertion.

Purpose

For the temporary relief of minor muscle or joint aches and pain; strains, sprains, bruises, backache or overexertion.

Warning

Warning: Do not take this product for pain for more than 10 days for adults or 5 days for children unless directed by a doctor.

When Using

When using this product if pain persists or gets worse, if new symptoms occur, or if redness or swelling is present, consult a doctor because these could be signs of a serious condition.

Pregnancy and Breast Feeding

If pregnant or breast-feeding, ask a health professional before use.

Keep Out of Reach of Children

Overdosage

In case of overdose, seek medical help or contact a Poison Control Center immediately.